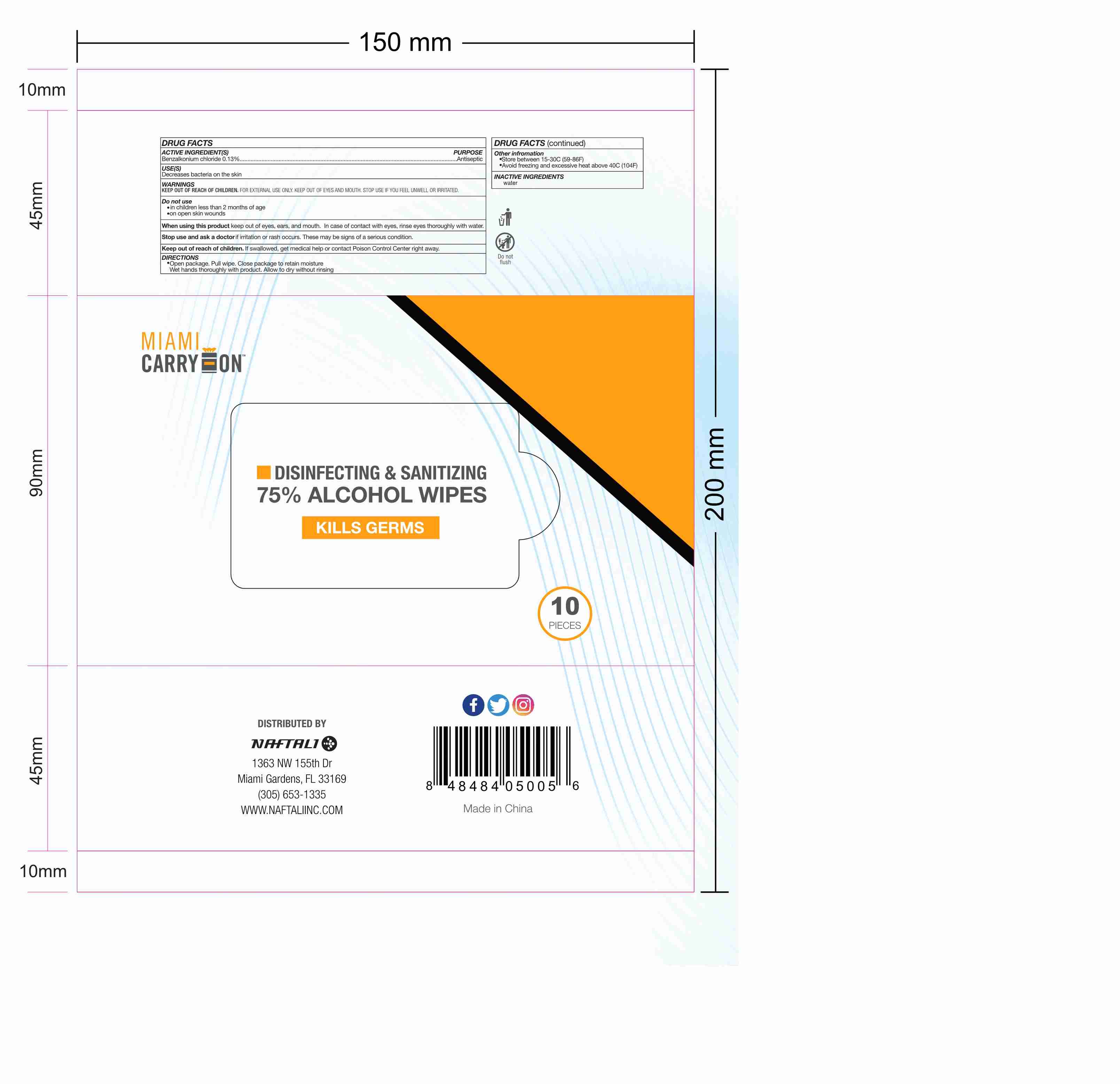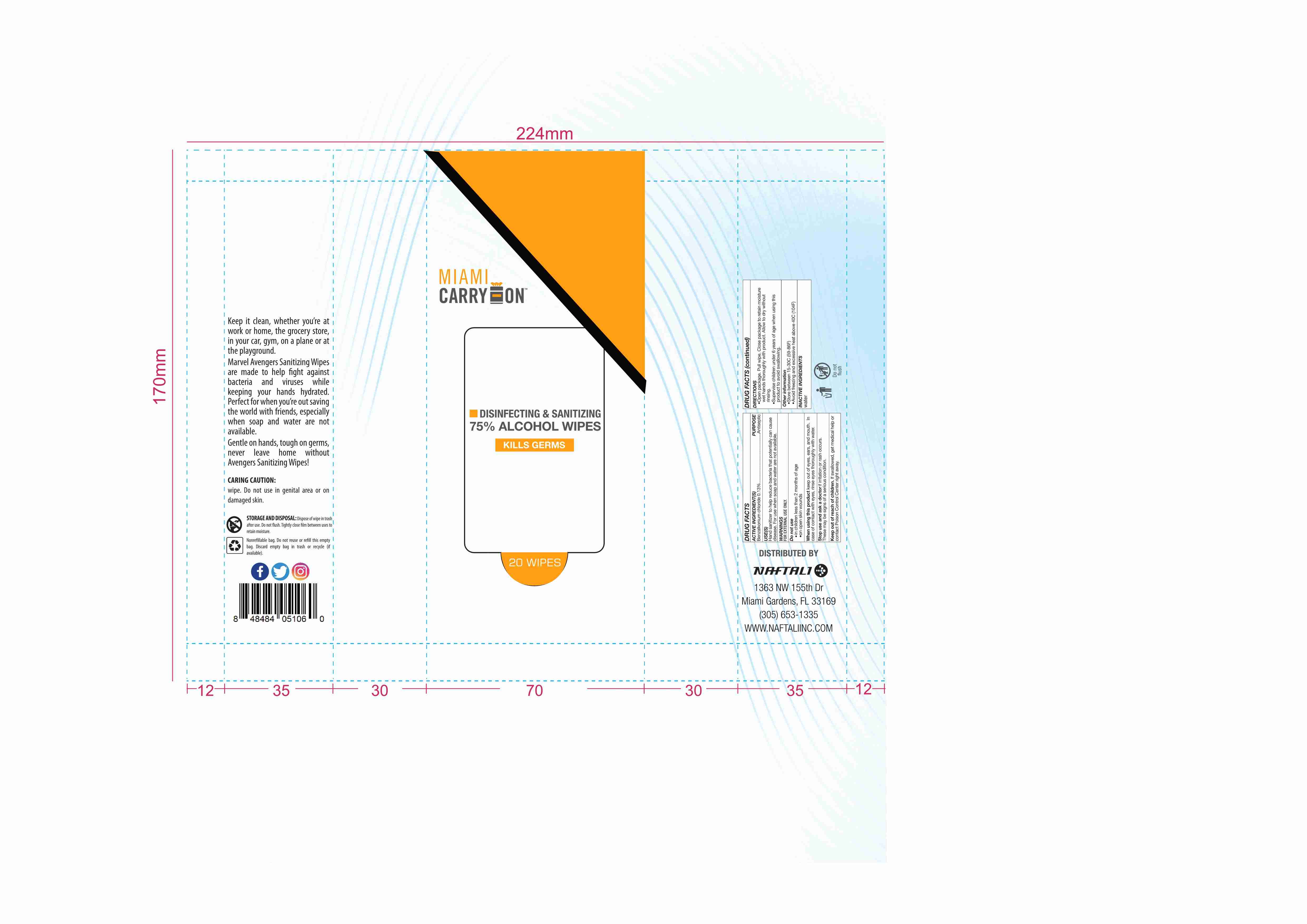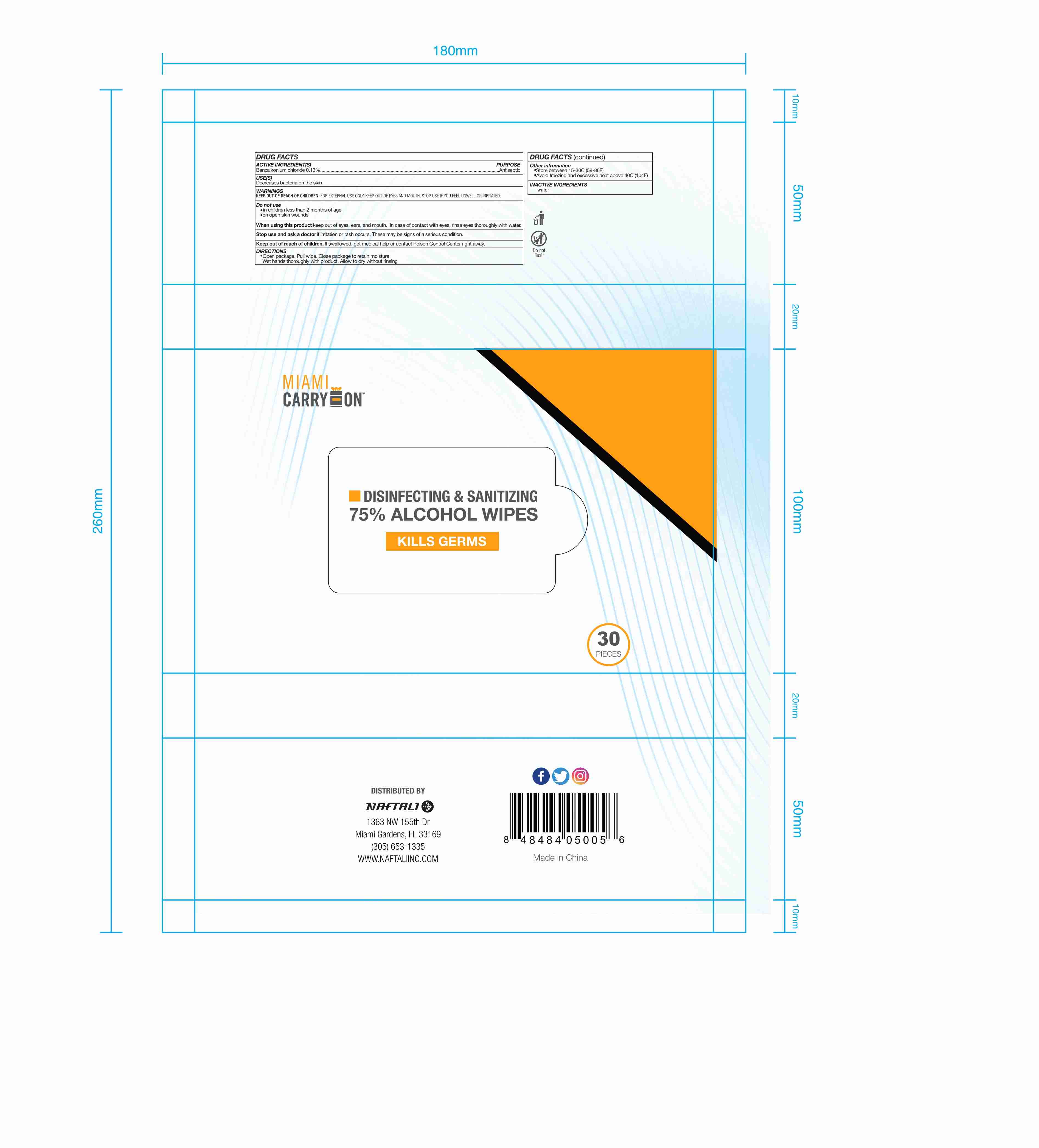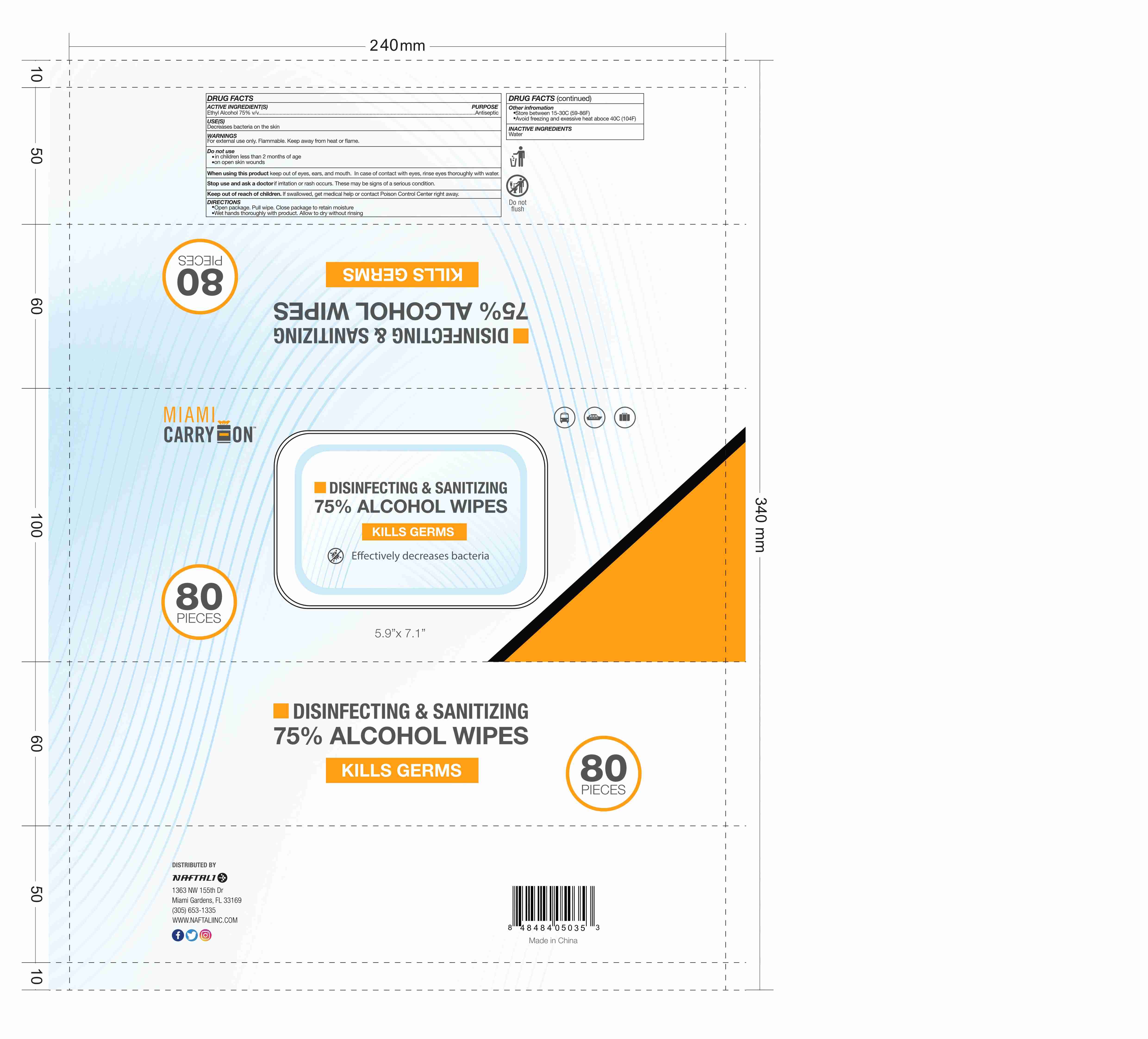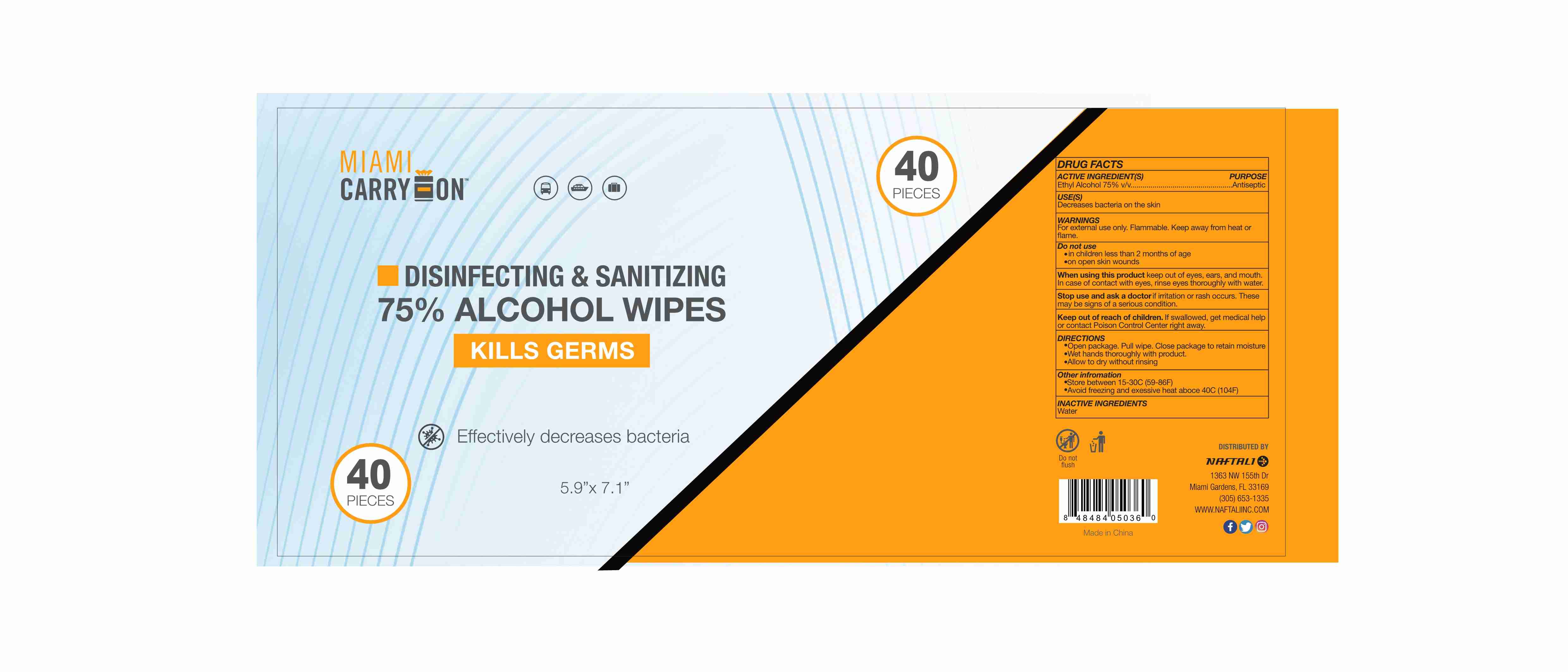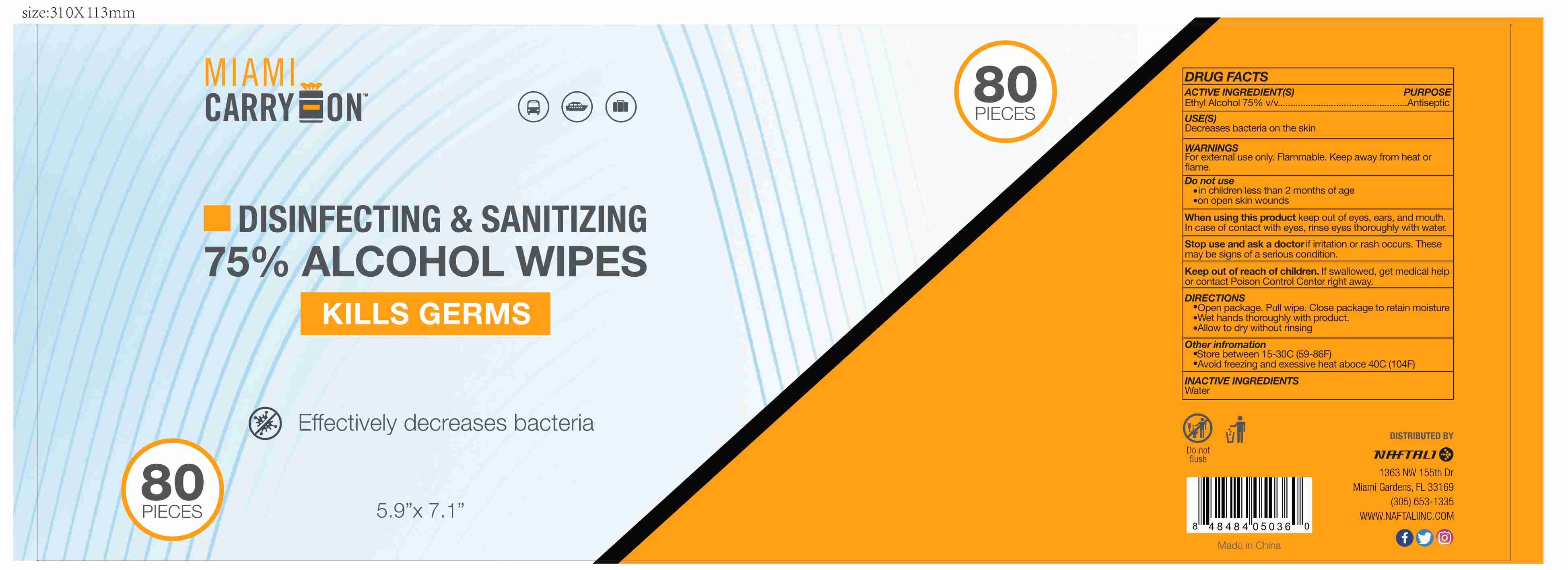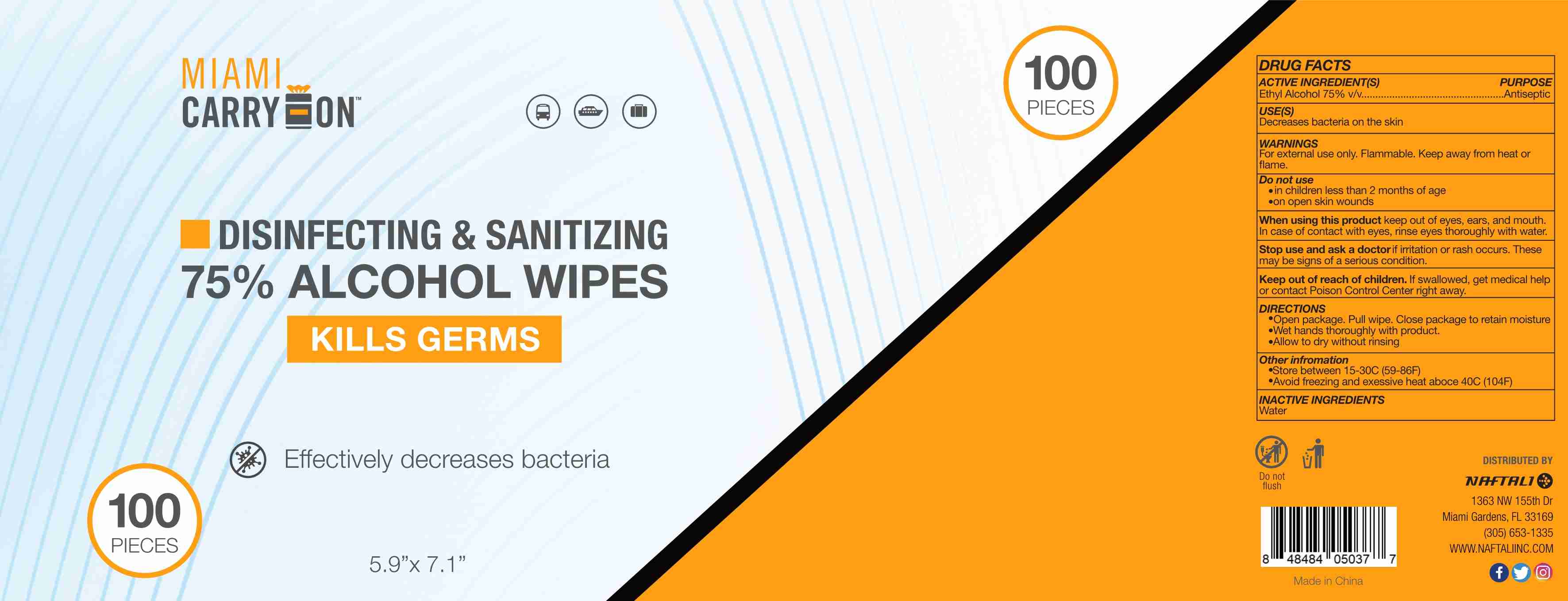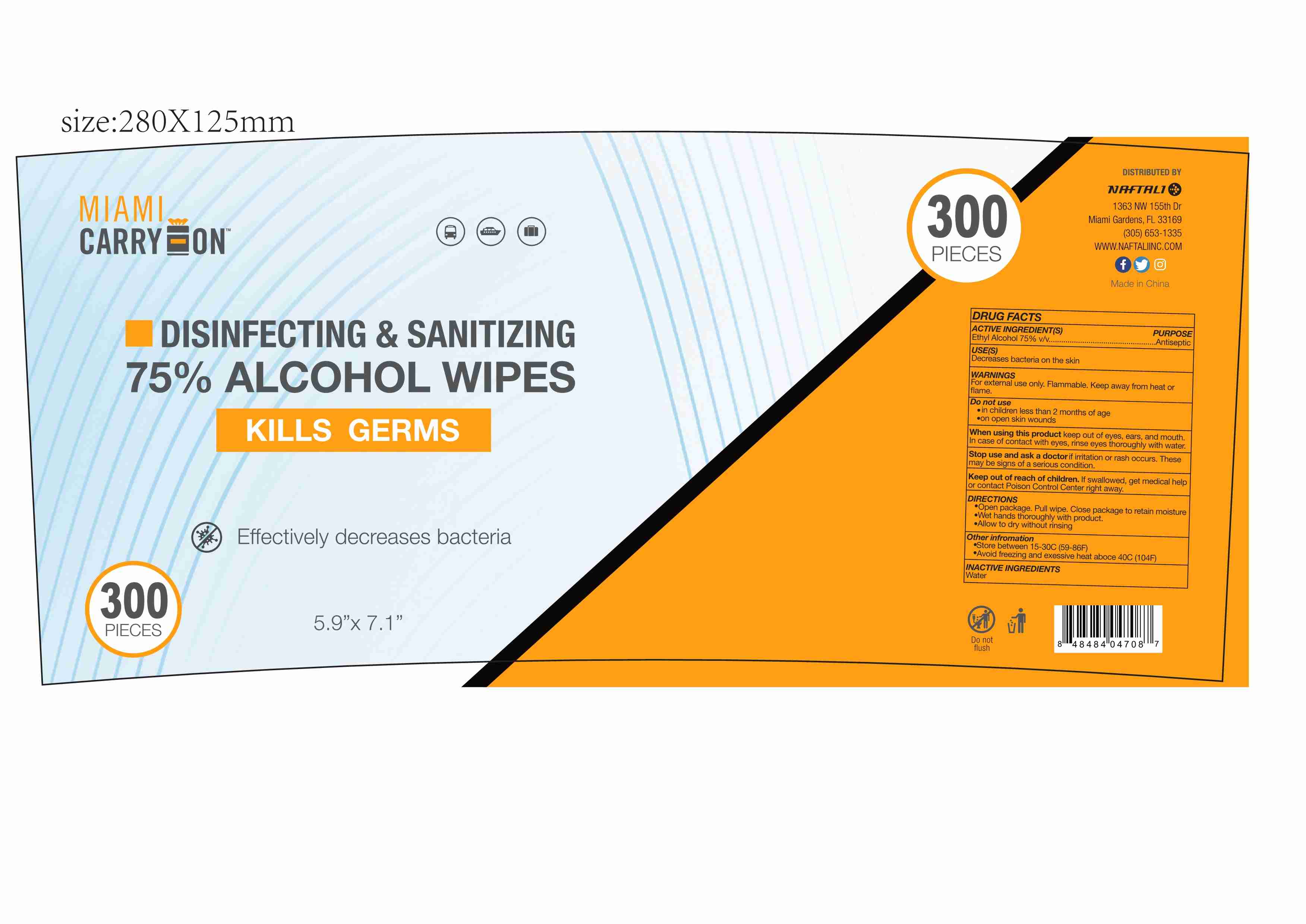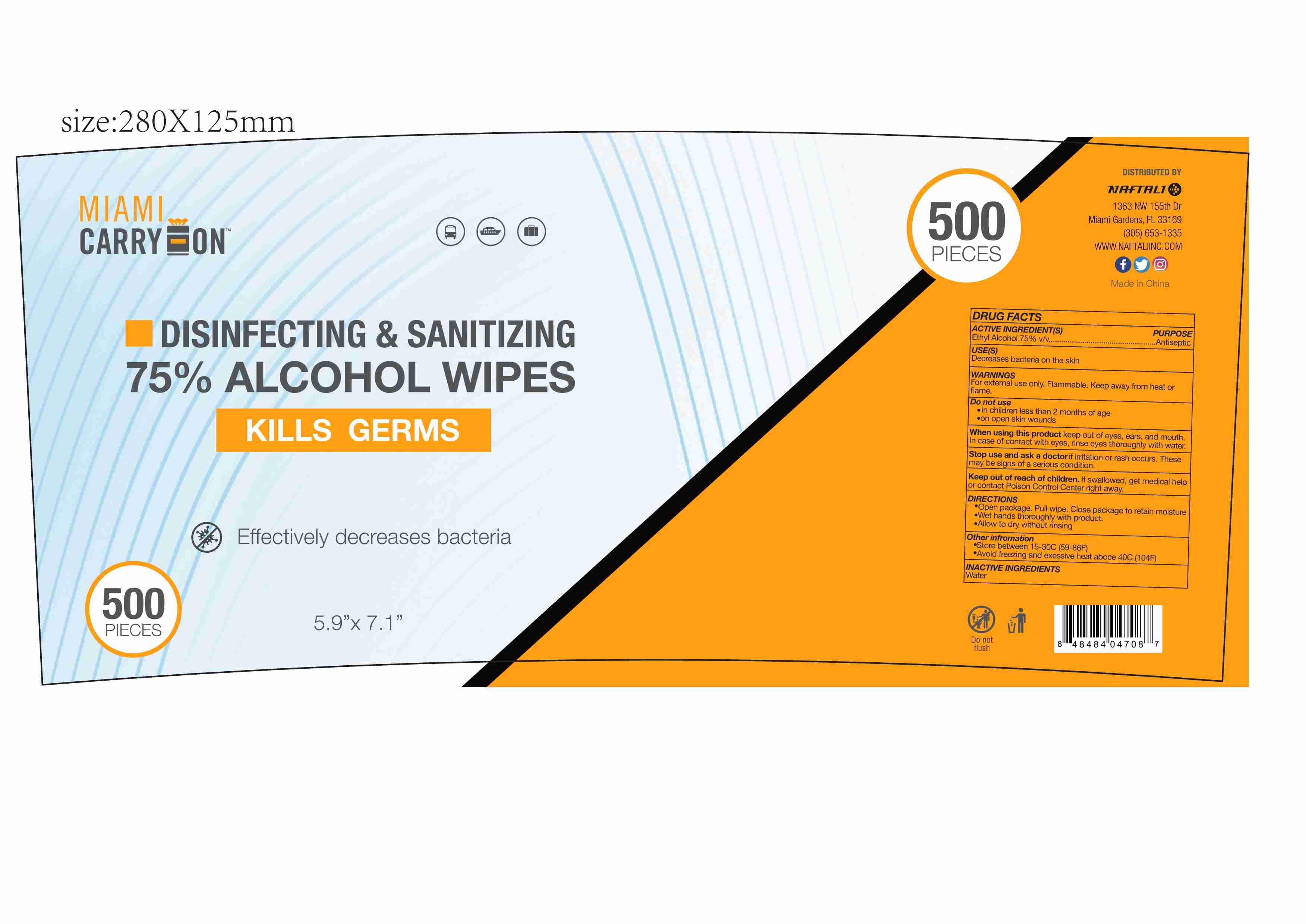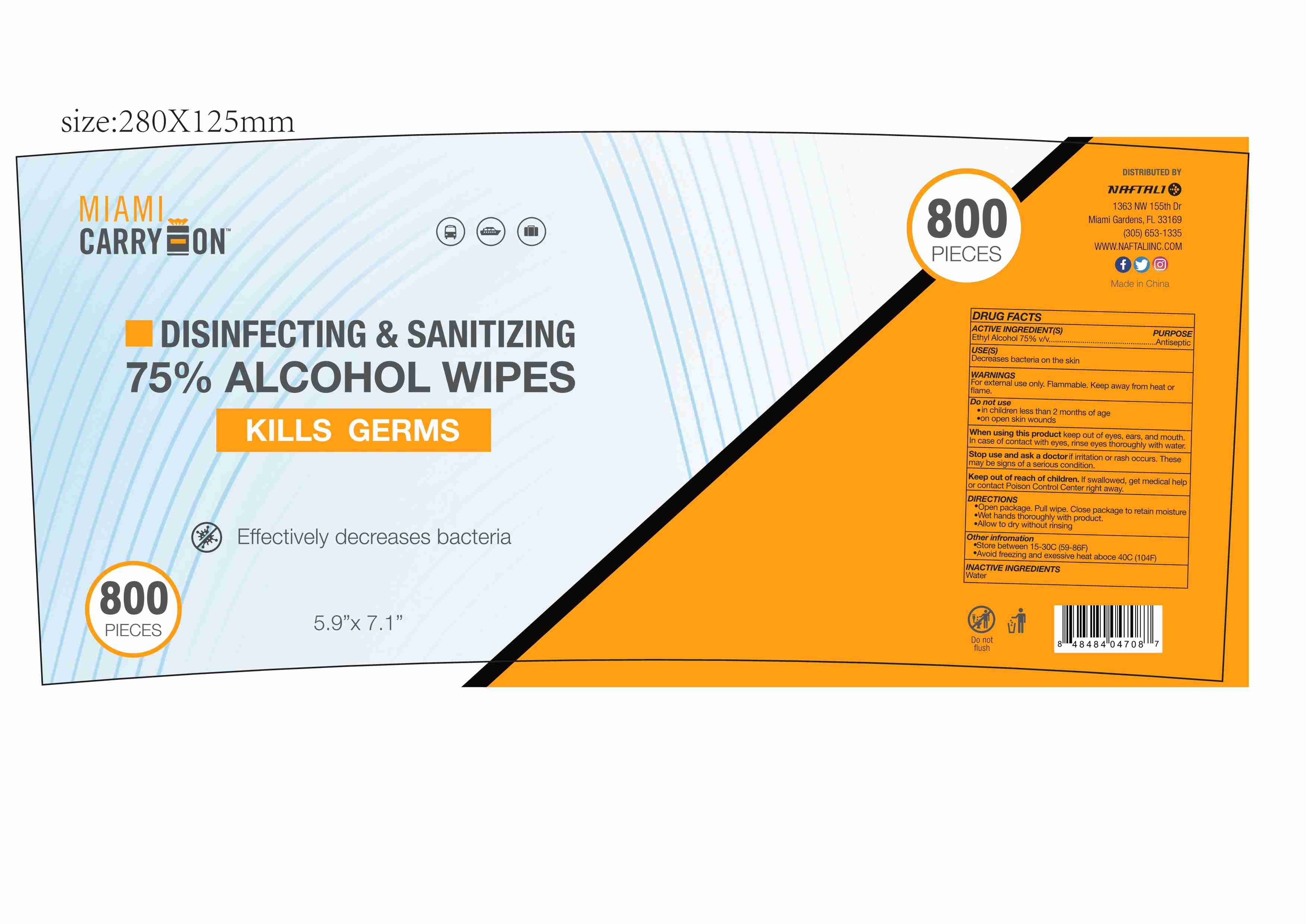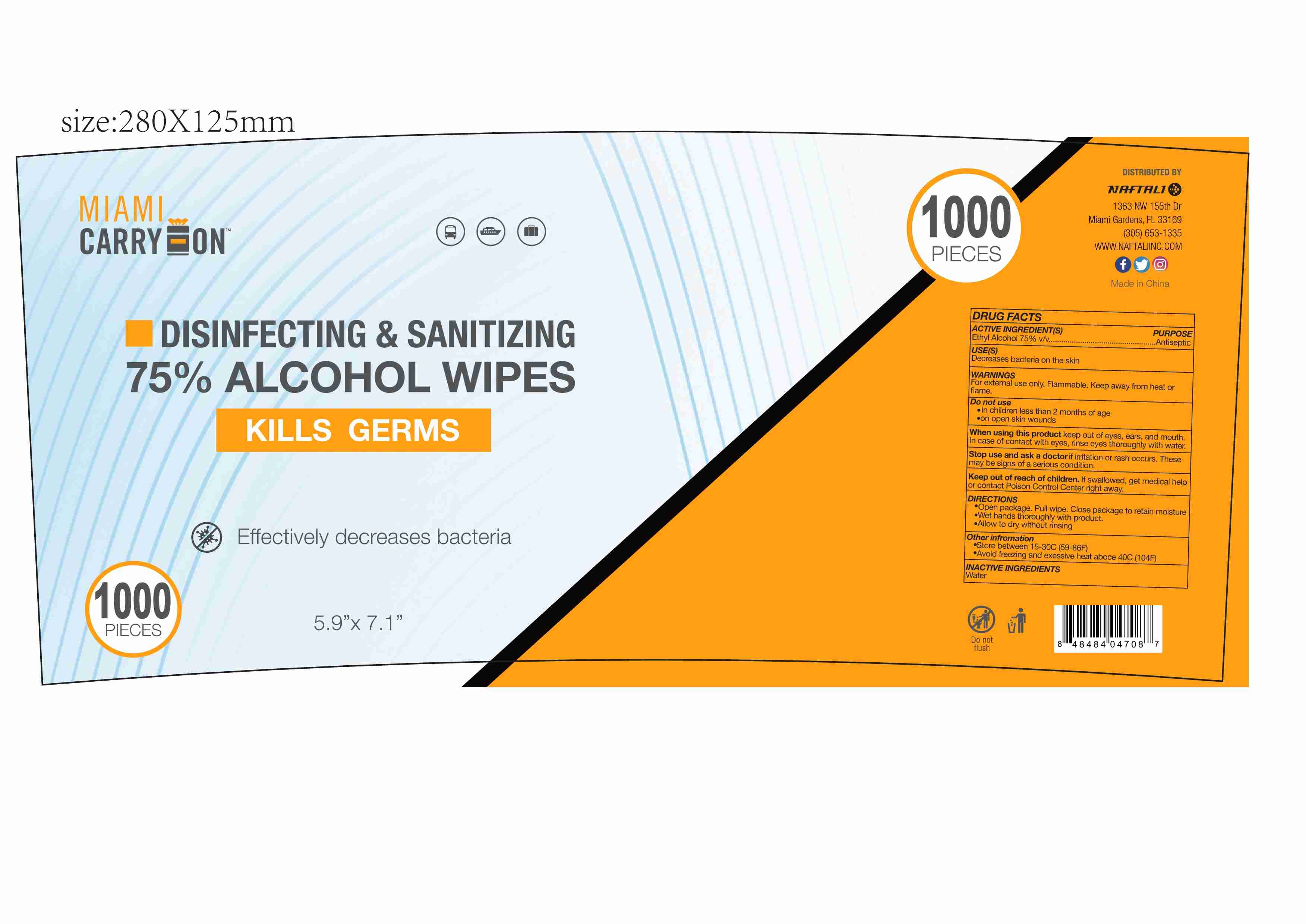 DRUG LABEL: DISINFECTING SANITIZING WIPES
NDC: 80593-005 | Form: SOLUTION
Manufacturer: ZHANGZHOU WANSIKE ELECTRONICS CO., LTD
Category: otc | Type: HUMAN OTC DRUG LABEL
Date: 20201209

ACTIVE INGREDIENTS: ALCOHOL 75 mL/100 1
INACTIVE INGREDIENTS: WATER

80593-005
DISINFECTING&SANITIZING WIPES

Active Ingredient(s)

Ethyl Alcohol 75% v/v

Purpose

Antiseptic

Use

Decreases bacteria on the skin

Warnings

For external use only. Flammable. Keep away from heat or flame.

Do not use

in children less than 2 months of age
on open skin wounds

When using this product keep out of eyes, ears, and mouth.
In case of contact with eyes, rinse eyes thoroughly with water.

Keep out of reach of children. If swallowed, get medical help or contact Poison Control Center right away.

Directions

Open package. Pull wipe. Close package to retain moisture
Wet hands thoroughly with product.
Allow to dry without rinsing

Other information

Store between 15-30C (59-86F)
Avoid freezing and exessive heat aboce 40C (104F)

Inactive ingredients

Water